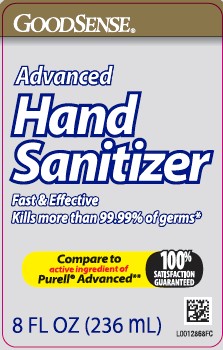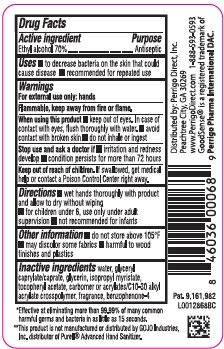 DRUG LABEL: Advanced
NDC: 75981-370 | Form: GEL
Manufacturer: Perrigo Direct, Inc
Category: otc | Type: HUMAN OTC DRUG LABEL
Date: 20260219

ACTIVE INGREDIENTS: ALCOHOL 70 mL/100 mL
INACTIVE INGREDIENTS: WATER; GLYCERYL CAPRYLATE/CAPRATE; GLYCERIN; ISOPROPYL MYRISTATE; .ALPHA.-TOCOPHEROL ACETATE; CARBOMER HOMOPOLYMER, UNSPECIFIED TYPE; CARBOMER COPOLYMER TYPE A (ALLYL PENTAERYTHRITOL CROSSLINKED); SULISOBENZONE

Good Sense 370.001/370AE Rev 2
Advanced Hand Sanitizer

Active ingredient

Ethyl Alcohol 70%

Purpose

Antiseptic

Uses

- to decrease bacteria on the skin that could cause disease
- recommended for repeated use

Warnings

For external use only: hands

Flammable, keep away from fire or flame.

When using this product

- keep out of eyes. In case of contact with eyes, flush thoroughly with water.
- avoid contact with broken skin
- do not inhale or ingest

Stop use and ask a doctor if

- irritation and redness develop
- condition persists for more than 72 hours

Keep out of reach of children.

If swallowed, get medical help or contact a Poison Control Center right away.

Directions

- wet hands thoroughly with product and allow to dry without wiping
- for children under 6, use only under adult supervision
- not recommended for infants

Other information

- do not store above 105⁰F
- may discolor some fabrics
- harmful to wood finishes and plastics

Inactive ingredients

water, glyceryl caprylate/caprate, glycerin, isopropyl myristate, tocopheryl acetate, carbomer or acrylates/C10-30 alkyl acrylate crosspolymer, fragrance, benzophenone-4

Claims

*Effective at eliminating more than 99.99% of may comon harmful germs and bacteria in as little as 15 seconds.

Disclaimer

**This product is not manufactured or distributed by GOJO Industries, Inc., distributor of PurellAdvanced Hand Sanitizer.

ADVERSE REACTION

Distributed By: Perrigo Direct, Inc.

Peachtree City, GA 30269

www.PerigoDirect.com

1-888-593-0593

GoodSenseis a registered trademark of Perrigo Pharma International DAC.

Principal display panel

GOODSENSE®

Advanced

Hand Sanitizer

Fast & Effective

Kills more than 99.99% of germs*

Compare to active ingredient of Purell®Advanced**

100% SATISFACTION GUARANTEED

8 FL OZ (236 mL)